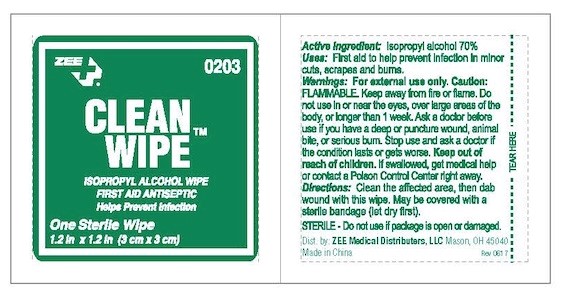 DRUG LABEL: Zee Medical Clean Wipes
NDC: 42961-018 | Form: SPONGE
Manufacturer: Cintas Corporation
Category: otc | Type: HUMAN OTC DRUG LABEL
Date: 20210924

ACTIVE INGREDIENTS: ISOPROPYL ALCOHOL .7 1/.7 mL
INACTIVE INGREDIENTS: WATER

Zee Clean Wipes

Warnings

For External use only. Caution: FLAMMABLE. Keep away from fire or flame.

Do not use

- in the eyes
- longer than 1 week
- over large areas of the body

Ask a doctor before use if you have

- deep or puncture wound
- animal bite
- serious burn

Stop use and ask a doctor if the condition lasts or gets worse

KEEP OUT OF REACH OF CHILDREN

If swallowed, get medical help or contact a Poison Control Center right away.

Uses

First aid to help prevent infection in minor
cuts
scrapes
burns

Active Ingredients

Isopropyl aclcohol 70%

Inactive ingredients

deionized water

PURPOSE

Topical antiseptic

DOSAGE AND ADMINISTRATION

CLean the affected area, then dab wound with this wipe. May be covered with a sterile bandage (let dry first).

Questions?

1-877-327-2704 M-F 8am-4pm